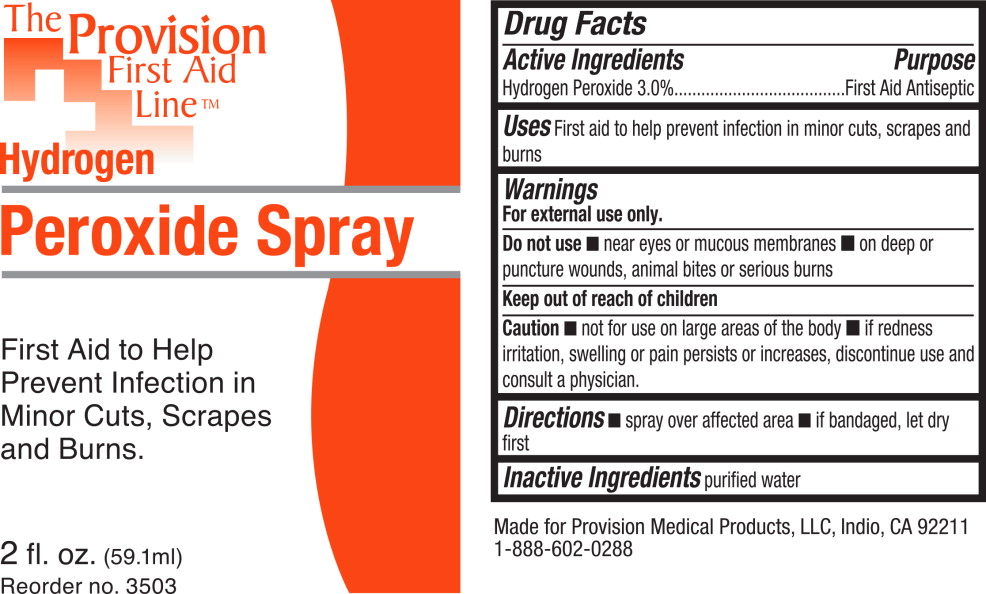 DRUG LABEL: Hydrogen Peroxide
NDC: 69103-5400 | Form: SPRAY
Manufacturer: Provision Medical
Category: otc | Type: HUMAN OTC DRUG LABEL
Date: 20131111

ACTIVE INGREDIENTS: hydrogen peroxide 30 mL/1 L
INACTIVE INGREDIENTS: water

Drug Facts

Active Ingredients

Hydrogen Peroxide 3.0%

Purpose

First Aid Antiseptic

Uses

First aid to help prevent infection in minor cuts, scrapes and burns

Warnings

For external use only.

Do not use

- near eyes or mucous membranes
- on deep or puncture wounds, animal bites or serious burns

Keep out of reach of children

Caution

- not for use on large areas of the body
- if redness irritation, swelling or pain persists or increases, discontinue use and consult a physician.

Directions

- spray over affected area
- if bandaged, let dry first

Inactive Ingredients

purified water

Principal Display Panel – 2 fl. oz Bottle Label

The Provision
First Aid
Line™

Hydrogen
Peroxide Spray

First Aid to Help
Prevent Infection in
Minor Cuts, Scrapes
and Burns.

2 fl. oz. (59.1 ml)

Reorder no. 3503